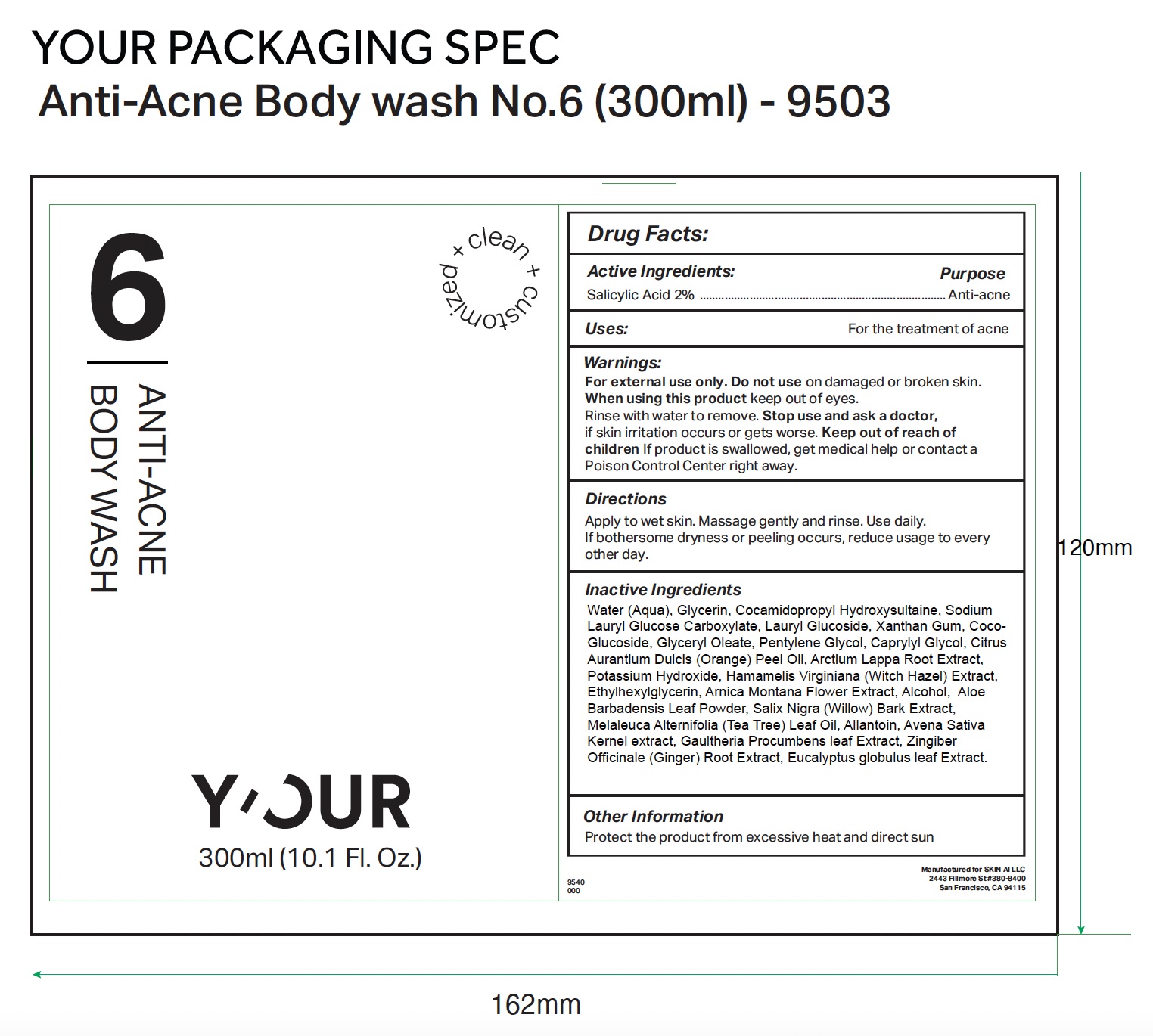 DRUG LABEL: YOUR Anti-Acne Body Wash
NDC: 84229-0018 | Form: LIQUID
Manufacturer: Skin Ai, LLC
Category: otc | Type: HUMAN OTC DRUG LABEL
Date: 20250210

ACTIVE INGREDIENTS: SALICYLIC ACID 2 g/100 mL
INACTIVE INGREDIENTS: SODIUM LAURYL GLYCOL CARBOXYLATE; ALLANTOIN; ZINGIBER OFFICINALE (GINGER) ROOT OIL; MELALEUCA ALTERNIFOLIA (TEA TREE) LEAF OIL; XANTHAN GUM; ARNICA MONTANA FLOWER; ALOE BARBADENSIS LEAF POWDER; OAT; GAULTHERIA PROCUMBENS LEAF; WATER; GLYCERIN; POTASSIUM HYDROXIDE; ETHYLHEXYLGLYCERIN; PENTYLENE GLYCOL; GLYCERYL OLEATE; CAPRYLYL GLYCOL; CITRUS AURANTIUM DULCIS (ORANGE) PEEL OIL; ARCTIUM LAPPA ROOT; COCO-GLUCOSIDE; COCAMIDOPROPYL HYDROXYSULTAINE; LAURYL GLUCOSIDE; HAMAMELIS VIRGINIANA LEAF; EUCALYPTUS GLOBULUS LEAF; ALCOHOL; SALIX NIGRA BARK

YOUR Anti Acne Body Wash 300 ml (10.1 fl oz)

Active ingredient

Salicylic Acid 2%

Purpose

Anti-acne

Uses

For the treatment of acne

Warnings

- For external use only

Do not use

on damaged or broken skin.

When using this product

keep out of eyes. Rinse with water to remove.

Stop use and ask a doctor

if skin irritation occurs or gets worse.

Keep out of reach of children.

If product is swallowed, get medical help or contact a Poison Control Center right away.

Directions

Apply to wet skin. Massage gently and rinse. Use daily. If bothersome dryness or peeling occurs, reduce usage to every other day.

Inactive ingredients

Water (Aqua), Glycerin, Cocamidopropyl Hydroxysultaine, Sodium Lauryl Glucose Carboxylate, Lauryl Glucoside, Xanthan Gum, Coco-Glucoside, Glyceryl Oleate, Pentylene Glycol, Caprylyl Glycol, Citrus Aurantium Dulcis (Orange) Peel Oil, Arctium Lappa (Burdock) Root Extract, Potassium Hydroxide, Hamamelis Virginiana (Witch Hazel) Extract, Ethylhexylglycerin, Arnica Montana Flower Extract, Alcohol, Aloe Barbadensis Leaf Powder, Salix Nigra (Willow) Bark Extract, Melaleuca Alternifolia (Tea Tree) Leaf Oil, Allantoin, Avena Sativa (Oat) Kernel Extract, Gaultheria Procumbens (Wintergreen) Oil, Zingiber Officinale (Ginger) Root Extract, Eucalyptus Globulus (Eucalyptus) Leaf Oil.

Other information

Protect the product from excessive heat and direct sun.

Principal Display Panel

clean + customized

6

ANTI-ACNE

BODY WASH

Y'OUR

300 ml (10.1 Fl. Oz.)